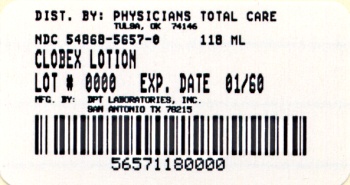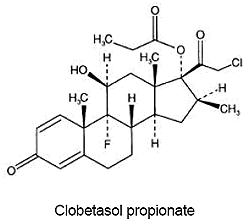 DRUG LABEL: Clobex
NDC: 54868-5657 | Form: LOTION
Manufacturer: Physicians Total Care, Inc.
Category: prescription | Type: HUMAN PRESCRIPTION DRUG LABEL
Date: 20110207

ACTIVE INGREDIENTS: CLOBETASOL PROPIONATE 0.05 mL/100 mL
INACTIVE INGREDIENTS: PROPYLENE GLYCOL; MINERAL OIL; CARBOMER 1342; SODIUM HYDROXIDE; WATER

DESCRIPTION

CLOBEX® (clobetasol propionate) Lotion, 0.05% contains clobetasol propionate, a synthetic fluorinated corticosteroid, for topical dermatologic use. The corticosteroids constitute a class of primarily synthetic steroids used topically as anti-inflammatory and antipruritic agents.

Clobetasol propionate is 21-chloro-9-fluoro-11β,17-dihydroxy-16β-methylpregna-1,4-diene-3, 20-dione17-propionate, with the empirical formula C25H32CIFO5, a molecular weight of 466.98 (CAS Registry Number 25122-46-7).

The following is the chemical structure:

Clobetasol propionate is a white to practically-white crystalline powder insoluble in water.

Each gram of CLOBEX® (clobetasol propionate) Lotion, 0.05% contains 0.5 mg of clobetasol propionate, in a vehicle base composed of hypromellose, propylene glycol, mineral oil, polyoxyethylene glycol 300 isostearate, carbomer 1342, sodium hydroxide and purified water.

CLINICAL PHARMACOLOGY

Like other topical corticosteroids, CLOBEX® (clobetasol propionate) Lotion, 0.05% has anti-inflammatory, antipruritic, and vasoconstrictive properties. The mechanism of the anti-inflammatory activity of the topical steroids in general is unclear. However, corticosteroids are thought to act by induction of phospholipase A2 inhibitory proteins, collectively called lipocortins. It is postulated that these proteins control the biosynthesis of potent mediators of inflammation such as prostaglandins and leukotrienes by inhibiting the release of their common precursor, arachidonic acid. Arachidonic acid is released from membrane phospholipids by phospholipase A2.

Pharmacokinetics

The extent of percutaneous absorption of topical corticosteroids is determined by many factors, including the vehicle, the integrity of the epidermal barrier and occlusion. For example, occlusive dressing with hydrocortisone for up to 24 hours has not been demonstrated to increase penetration; however, occlusion of hydrocortisone for 96 hours markedly enhances penetration. Topical corticosteroids can be absorbed from normal intact skin. Inflammation and other disease processes in the skin may increase percutaneous absorption.

There are no human data regarding the distribution of corticosteroids to body organs following topical application. Nevertheless, once absorbed through the skin, topical corticosteroids are handled through pharmacokinetic pathways similar to systematically administered corticosteroids. Due to the fact that circulating levels are usually below the level of detection, the use of pharmacodynamic endpoints for assessing the systemic exposure of topical corticosteroids is necessary. They are metabolized, primarily in the liver, and are then excreted by the kidneys. In addition, some corticosteroids and their metabolites are also excreted in the bile.

CLOBEX® (clobetasol propionate) Lotion, 0.05% is in the super-high range of potency as compared with other topical corticosteroids in vasoconstrictor studies.

In studies evaluating the potential for hypothalamic-pituitary-adrenal (HPA) axis suppression, CLOBEX® Lotion, 0.05% demonstrated rates of suppression that were numerically higher than those of a clobetasol propionate 0.05% cream (Temovate E® Emollient, 0.05%), (See PRECAUTIONS).

CLINICAL STUDIES

The efficacy of CLOBEX® (clobetasol propionate) Lotion, 0.05% in psoriasis and atopic dermatitis has been demonstrated in two adequate and well-controlled clinical trials. The first study was conducted in patients with moderate to severe plaque psoriasis. Patients were treated twice daily for 4 weeks with either CLOBEX® (clobetasol propionate) Lotion, 0.05% or vehicle lotion. Study results demonstrated that the efficacy of CLOBEX® Lotion, 0.05% in treating moderate to severe plaque psoriasis was superior to that of vehicle.

At the end of treatment (4 weeks), 30 of 82 patients (36.6%) treated with CLOBEX® Lotion, 0.05% compared with 0 of 29 (0%) treated with vehicle achieved success. Success was defined as a score of none or very mild (no or very slight clinical signs or symptoms of erythema, plaque elevation, or scaling) on the Global Severity scale of psoriasis.

The second study was conducted in patients with moderate to severe atopic dermatitis. Patients were treated twice daily for 2 weeks with either CLOBEX® (clobetasol propionate) Lotion, 0.05% or vehicle lotion. Study results demonstrated that the efficacy of CLOBEX® Lotion, 0.05% in treating moderate to severe atopic dermatitis was superior to that of vehicle.

At the end of treatment (2 weeks), 41 of 96 patients (42.7%) treated with CLOBEX® Lotion, 0.05% compared with 4 of 33 (12.1%) treated with vehicle achieved success. Success was defined as a score of none or very mild (no or very slight clinical signs or symptoms of erythema, induration/papulation, oozing/crusting, or pruritus) on the Global Severity scale of atopic dermatitis.

INDICATIONS AND USAGE

CLOBEX® (clobetasol propionate) Lotion, 0.05% is a super-high potent corticosteroid formulation indicated for the relief of the inflammatory and pruritic manifestations of corticosteroid-responsive dermatoses only in patients 18 years of age or older (see PRECAUTIONS). Treatment should be limited to 2 consecutive weeks. The total dosage should not exceed 50 g (50 mL or 1.75 fl.oz.) per week.

For the treatment of moderate to severe plaque psoriasis, localized lesions (less than 10% body surface area) that have not sufficiently improved after the initial 2-week treatment with CLOBEX® (clobetasol propionate) Lotion, 0.05% may be treated for up to 2 additional weeks. Any additional benefits of extending treatment should be weighed against the risk of HPA axis suppression before prescribing for more than 2 weeks.

Patients should be instructed to use CLOBEX® (clobetasol propionate) Lotion, 0.05% for the minimum amount of time necessary to achieve the desired results (see PRECAUTIONS).

Use in patients younger than 18 years of age is not recommended due to numerically high rates of HPA axis suppression (see PRECAUTIONS: Pediatric Use).

CONTRAINDICATIONS

CLOBEX® (clobetasol propionate) Lotion, 0.05% is contraindicated in patients who are hypersensitive to clobetasol propionate, to other corticosteroids, or to any ingredient in this preparation.

PRECAUTIONS

General

Clobetasol propionate is a highly potent topical corticosteroid that has been shown to suppress the HPA axis at the lowest doses tested.

Systemic absorption of topical corticosteroids has caused reversible adrenal suppression with the potential for glucocorticosteroid insufficiency after withdrawal of treatment. Manifestations of Cushing’s syndrome, hyperglycemia, and glucosuria can also be produced in some patients by systemic absorption of topical corticosteroids while on treatment.

Conditions which increase systemic absorption include the application of the more potent steroids, use over large surface areas, prolonged use, and the addition of occlusive dressings. Therefore, patients applying a topical steroid to a large surface area or to areas under occlusion should be evaluated periodically for evidence of adrenal suppression (see laboratory tests below). If adrenal suppression is noted, an attempt should be made to withdraw the drug, to reduce the frequency of application, or to substitute a less potent steroid. Recovery of HPA axis function is generally prompt upon discontinuation of topical corticosteroids. Infrequently, signs and symptoms of glucocorticosteroid insufficiency may occur requiring supplemental systemic corticosteroids. For information on systemic supplementation, see prescribing information for those products.

The effect of CLOBEX® Lotion, 0.05% on HPA axis function was compared to clobetasol propionate cream 0.05% (Temovate E® Emollient, 0.05%) in adults in two studies, one for psoriasis and one for atopic dermatitis. In total, 8 of 10 evaluable patients with moderate to severe plaque psoriasis experienced adrenal suppression following 4 weeks of CLOBEX® Lotion, 0.05% therapy (treatment beyond 4 consecutive weeks is not recommended in moderate to severe plaque psoriasis). In follow-up testing, 1 of 2 patients remained suppressed after 8 days. In this comparative study, for clobetasol propionate cream, 0.05% there were 3 of 10 evaluable patients with HPA axis suppression. Furthermore, 5 of 9 evaluable patients with moderate to severe atopic dermatitis experienced adrenal suppression following 2 weeks of CLOBEX® Lotion, 0.05% therapy (treatment beyond 2 consecutive weeks is not recommended in moderate to severe atopic dermatitis). Of the 3 patients that had follow-up testing, one patient failed to recover adrenal function 7 days post-treatment. For patients treated with clobetasol propionate cream, 0.05%, 4 of 9 evaluable patients experienced adrenal suppression following 2 weeks of treatment. Of the 2 patients that had follow-up testing, both recovered adrenal function 7 days post-treatment. The proportion of subjects suppressed may be underestimated because the adrenal glands were stimulated weekly with cosyntropin in these studies.

The potential increase in systemic exposure does not correlate with any proven benefit, but may lead to an increased potential for hypothalamic-pituitary-adrenal (HPA) axis suppression. Patients with acute illness or injury may have increased morbidity and mortality with intermittent HPA axis suppression. Patients should be instructed to use CLOBEX® Lotion, 0.05% for the minimum amount of time necessary to achieve the desired results (See INDICATIONS AND USAGE).

If irritation develops, CLOBEX® Lotion, 0.05% should be discontinued and appropriate therapy instituted. Allergic contact dermatitis with corticosteroids is usually diagnosed by observing a failure to heal rather than noting a clinical exacerbation, as with most topical products not containing corticosteroids.

In the presence of dermatological infections, the use of an appropriate antifungal or antibacterial agent should be instituted. If a favorable response does not occur promptly, use of CLOBEX® Lotion, 0.05% should be discontinued until the infection has been adequately controlled.

CLOBEX® Lotion, 0.05% should not be used in the treatment of rosacea or perioral dermatitis, and should not be used on the face, groin, or axillae.

Information for Patients

Patients using topical corticosteroids should receive the following information and instructions:

- This medication is to be used as directed by the physician and should not be used longer than the prescribed time period.
- This medication should not be used for any disorder other than that for which it was prescribed.
- The treated skin area should not be bandaged, otherwise covered, or wrapped so as to be occlusive unless directed by the physician.
- Patients should wash their hands after applying the medication.
- Patients should report any signs of local or systemic adverse reactions to the physician.
- Patients should inform their physicians that they are using CLOBEX® (clobetasol propionate) Lotion, 0.05% if surgery is contemplated.
- This medication is for external use only. It should not be used on the face, underarms, or groin area, and avoid contact with the eyes and lips.
- As with other corticosteroids, therapy should be discontinued when control is achieved. If no improvement is seen within 2 weeks, contact the physician.
- Patients should be informed to not use more than 50 g (50 mL or 1.75 fl.oz.) per week of CLOBEX® Lotion, 0.05%.

Laboratory Tests

The following tests may be helpful in evaluating patients for HPA axis suppression:

- Cosyntropin stimulation test
- AM plasma cortisol test
- Urinary free cortisol test

Carcinogenesis, Mutagenesis, Impairment of Fertility

Long-term animal studies have not been performed to evaluate the carcinogenic potential of clobetasol propionate.

Clobetasol propionate was non-mutagenic in three different test systems: the Ames test, the Saccharomyces cerevisiae gene conversion assay, and the E. coli B WP2 fluctuation test.

Studies in the rat following subcutaneous administration at dosage levels up to 50 μg/kg per day revealed that the females exhibited an increase in the number of resorbed embryos and a decrease in the number of living fetuses at the highest dose.

Pregnancy Teratogenic effects Pregnancy Category C

Corticosteroids have been shown to be teratogenic in laboratory animals when administered systemically at relatively low dosage levels. Some corticosteroids have been shown to be teratogenic after dermal application to laboratory animals.

Clobetasol propionate is absorbed percutaneously, and when administered subcutaneously it was a significant teratogen in both the rabbit and the mouse. Clobetasol propionate has greater teratogenic potential than steroids that are less potent.

Teratogenicity studies in mice using the subcutaneous route resulted in fetotoxicity at the highest dose tested (1 mg/kg) and teratogenicity at all dose levels tested down to 0.03 mg/kg. These doses are approximately 1.4 and 0.04 times, respectively, the human topical dose of CLOBEX® (clobetasol propionate) Lotion, 0.05%. Abnormalities seen included cleft palate and skeletal abnormalities.

In rabbits, clobetasol propionate was teratogenic at doses of 3 and 10 μg/kg. These doses are approximately 0.02 and 0.05 times, respectively, the human topical dose of CLOBEX® (clobetasol propionate) Lotion, 0.05%. Abnormalities seen included cleft palate, cranioschisis, and other skeletal abnormalities.

A teratogenicity study in rats using the dermal route resulted in dose related maternal toxicity and fetal effects from 0.05 to 0.5 mg/kg/day of clobetasol propionate. These doses are approximately 0.14 to 1.4 times, respectively, the human topical dose of CLOBEX® (clobetasol propionate) Lotion, 0.05%. Abnormalities seen included low fetal weights, umbilical herniation, cleft palate, reduced skeletal ossification, and other skeletal abnormalities.

There are no adequate and well-controlled studies of the teratogenic potential of clobetasol propionate in pregnant women. CLOBEX® (clobetasol propionate) Lotion, 0.05% should be used during pregnancy only if the potential benefit justifies the potential risk to the fetus.

Nursing Mothers

Systemically administered corticosteroids appear in human milk and could suppress growth, interfere with endogenous corticosteroid production, or cause other untoward effects. It is not known whether topical administration of corticosteroids could result in sufficient systemic absorption to produce detectable quanitities in breast milk. Because many drugs are excreted in human milk, caution should be exercised when CLOBEX® Lotion, 0.05% is administered to a nursing woman.

Pediatric Use

Use of CLOBEX® Lotion, 0.05% in pediatric patients is not recommended due to the potential for HPA axis suppression (see PRECAUTIONS: General).

The HPA axis suppression potential of CLOBEX® Lotion, 0.05% has been studied in adolescents (12 to 17 years of age) with moderate to severe atopic dermatitis covering a minimum of 20% of the total body surface area. In total 14 patients were evaluated for HPA axis function. Patients were treated twice daily for 2 weeks with CLOBEX® Lotion, 0.05%. After 2 weeks of treatment, 9 out of 14 of the patients experienced adrenal suppression. One out of 4 patients treated with CLOBEX® Lotion, 0.05% who were retested remained suppressed two weeks post-treatment. In comparison, 2 of 10 of the patients treated with clobetasol propionate cream, 0.05% demonstrated HPA axis suppression. One patient who was retested recovered.

None of the patients who developed HPA axis suppression had concomitant clinical signs of adrenal suppression and none of them was discontinued from the study for reasons related to the safety or tolerability of CLOBEX® Lotion, 0.05%. However patients with acute illness or injury may have increased morbidity and mortality with intermittent HPA axis suppression.

Because of a higher ratio of skin surface area to body mass, pediatric patients are at a greater risk than adults of HPA axis suppression and Cushing’s syndrome when they are treated with topical corticosteroids. They are therefore also at greater risk of glucocorticosteroid insufficiency during and/or after withdrawal of treatment. Adverse effects including striae have been reported with inappropriate use of topical corticosteroids in infants and children.

HPA axis suppression, Cushing’s syndrome, linear growth retardation, delayed weight gain, and intracranial hypertension have been reported in children receiving topical corticosteroids. Manifestations of adrenal suppression in children include low plasma cortisol levels and absence of response to ACTH stimulation. Manifestations of intracranial hypertension include bulging fontanelles, headaches, and bilateral papilledema.

Geriatric Use

Clinical studies of CLOBEX® (clobetasol propionate) Lotion, 0.05% did not include sufficient numbers of patients aged 65 and over to determine whether they respond differently than younger patients. In general, dose selection for an elderly patient should be made with caution, usually starting at the low end of the dosing range, reflecting the greater frequency of decreased hepatic, renal or cardiac function, and of concomitant disease or other drug therapy.

ADVERSE REACTIONS

In controlled clinical trials with CLOBEX® (clobetasol propionate) Lotion, 0.05%, the following adverse reactions have been reported: burning/stinging, skin dryness, irritation, erythema, folliculitis, pruritus, skin atrophy, and telangiectasia.

The pooled incidence of local adverse reactions in trials for psoriasis and atopic dermatitis with CLOBEX® (clobetasol propionate) Lotion, 0.05% at 1.0% or greater was:

Adverse Reaction | Incidence
Skin Atrophy | 4.2%
Telangiectasia | 3.2%
Discomfort Skin | 1.3%
Skin Dry | 1.0%

Other local adverse events occurred at rates less than 1.0%. Similar rates of local adverse reactions were reported in the comparator (clobetasol propionate cream, 0.05%). Most local adverse events were rated as mild to moderate and they are not affected by age, race or gender.

The following additional local adverse reactions have been reported with topical corticosteroids. They may occur more frequently with the use of occlusive dressings and higher potency corticosteroids, including clobetasol propionate. These reactions are listed in an approximate decreasing order of occurrence: irritation, dryness, folliculitis, acneiform eruptions, hypopigmentation, perioral dermatitis, allergic contact dermatitis, secondary infection, striae and miliaria.

OVERDOSAGE

Topically applied CLOBEX® (clobetasol propionate) Lotion, 0.05% can be absorbed in sufficient amount to produce systemic effects. (See PRECAUTIONS).

DOSAGE AND ADMINISTRATION

CLOBEX® Lotion, 0.05% should be applied to the affected skin areas twice daily and rubbed in gently and completely. (See INDICATIONS AND USAGE.)

CLOBEX® Lotion, 0.05% contains a super-high potent topical corticosteroid; therefore treatment should be limited to:

- 2 consecutive weeks for the relief of the inflammatory and pruritic manifestations of corticosteroid-responsive dermatoses,

- and up to 2 additional weeks in very localized lesions of moderate to severe plaque psoriasis (no more than 10% body surface area) that have not sufficiently improved after the initial 2 weeks of treatment with CLOBEX® (clobetasol propionate) Lotion 0.05%.

The total dosage should not exceed 50 g (50 mL or 1.75 fl. oz.) per week because of the potential for the drug to suppress the hypothalamic-pituitary-adrenal (HPA) axis.

Therapy should be discontinued when control has been achieved. If no improvement is seen within 2 weeks, reassessment of diagnosis may be necessary.

Use in pediatric patients younger than 18 years is not recommended because of numerically high rates of HPA axis suppression (See PRECAUTIONS: Pediatric Use).

Unless directed by physician, CLOBEX® Lotion, 0.05% should not be used with occlusive dressings.

HOW SUPPLIED

CLOBEX® Lotion, 0.05% is supplied in the following sizes:

2 fl. oz./59 mL high density polyethylene bottles - NDC 54868-5657-1

4 fl. oz./118 mL high density polyethylene bottles - NDC 54868-5657-0

Store at controlled room temperature 68˚ to 77˚F (20˚-25˚C). Protect from freezing.

Marketed by:

GALDERMA LABORATORIES, L.P.

Fort Worth, Texas 76177 USA

Manufactured by:

DPT Laboratories, Ltd.

San Antonio, Texas 78215 USA

GALDERMA is a registered trademark.

Temovate E is a registered trademark of Glaxo SmithKline.

www.clobex.com

325067-1004

Revised: October 2004

CLOBEX®

(clobetasol propionate) Lotion, 0.05%

Relabeling of "Additional" barcode label by:

Physicians Total Care, Inc.

Tulsa, OK 74146

PATIENT INFORMATION

For External Use Only

Not for Ophthalmic (Eye) Use

Read the Patient Information that comes with CLOBEX® (KLO-bex) Lotion before you start using it and each time you get a refill. There may be new information. This leaflet does not take the place of talking with your doctor about your medical condition or your treatment.

What is CLOBEX® Lotion?

CLOBEX® Lotion is a medicine called a topical (skin use only) corticosteroid. It is used for a short time to reduce the inflammation and itching of:

• Moderate to severe skin conditions (atopic dermatitis and other skin problems)

• Moderate to severe plaque psoriasis

CLOBEX® Lotion is a super-high potent (very strong) topical corticosteroid. It is very important that you use CLOBEX® Lotion only as directed, in order to avoid serious side effects.

Who should not use CLOBEX® Lotion?

Do not use CLOBEX® Lotion if you are allergic to any of its ingredients, or to any other corticosteroid. The active ingredient is clobetasol propionate. See the end of this leaflet for the complete list of other ingredients in CLOBEX® Lotion. Ask your doctor or pharmacist if you need a list of other corticosteroids.

CLOBEX® Lotion is not recommended for use on anyone younger than 18 years of age. CLOBEX® Lotion has not been studied in children under 12 years old. Children have smaller body sizes and have a higher chance of side effects.

What should I tell my doctor before using CLOBEX® Lotion?

Tell your doctor:

- if you are pregnant, think you are pregnant or plan to be pregnant. Talk with your doctor before using CLOBEX® Lotion or if you are already using CLOBEX® Lotion, as it is not known if CLOBEX® Lotion can harm your unborn child.
- if you are breastfeeding. It is not known if CLOBEX® Lotion passes into your milk.
- if you think you have a skin infection. You may need another medicine to treat the skin infection before you use CLOBEX® Lotion.

Tell your doctor about all the other medicines and skin products you use, including prescription and non-prescription medicines, cosmetics, vitamins, and herbal supplements. Some medicines can cause serious side effects if used while you are using CLOBEX® Lotion.

How should I use CLOBEX® Lotion?

- Use CLOBEX® Lotion exactly as directed by your doctor. CLOBEX® Lotion is for skin use only.
- Apply CLOBEX® Lotion twice a day, once in the morning and once at night, or as directed by your doctor.
- Use only enough to cover the affected areas. Do not apply CLOBEX® Lotion to your face, neck, groin or armpits. Do not get CLOBEX® Lotion on your lips or in or near your eyes.
- Make sure your skin is clean and dry before applying CLOBEX® Lotion.
- Turn the bottle of CLOBEX® Lotion upside down. Pour a small amount, less than 1 teaspoonful of CLOBEX® Lotion onto your fingertips, or directly on your affected skin area. Gently, rub the CLOBEX® Lotion into your affected skin area, until the lotion disappears.
- Wash your hands after using CLOBEX® Lotion.
- If you forget to apply CLOBEX® Lotion at the scheduled time, use it as soon as you remember. Then go back to your regular schedule. If it is about time for your next dose, apply just that 1 dose, and continue with your normal application schedule. Do not try to make up for the missed dose. If you miss several doses, tell your doctor.
- Throw away unused CLOBEX® Lotion.

What should I avoid while using CLOBEX® Lotion?

Do not do the following while using CLOBEX® Lotion:

- Do not get CLOBEX® Lotion on your face, lips, or in or near your eyes because this might cause irritation. If you do, use a lot of water to rinse the CLOBEX® Lotion off your face, lips, or out of your eyes. If your eyes keep stinging after rinsing them well with water, call your doctor right away.
- Do not apply CLOBEX® Lotion to your groin or armpits.
- Do not bandage or cover your treated areas unless your doctor tells you to do so.
- Do not wear tight fitting clothes over your treated skin areas.
- Do not use CLOBEX® Lotion any longer than 2 weeks (14 days) for moderate to severe conditions (atopic dermatitis and other skin problems).
- Do not use CLOBEX® Lotion any longer than an extra 2 weeks (4 weeks total) for psoriasis on a small area of your body (less than 10 percent of your body surface area) that is not much better after the first 2 weeks of treatment.
- Do not use more than 50 grams (50 mL or 1.75 fluid ounces) of CLOBEX® Lotion a week. CLOBEX® Lotion comes in 2 different size bottles, a 2-ounce and a 4-ounce bottle.

What are the possible side effects of CLOBEX® Lotion?

CLOBEX® Lotion can pass through your skin. Too much CLOBEX® Lotion passing through your skin can shut down your adrenal glands.This usually happens if you use too much CLOBEX® Lotion, or you use it for too long. If this happens, your adrenal glands may not start working immediately once you stop using CLOBEX® Lotion. Shutting down of the adrenal glands can cause nausea, vomiting, fever, low blood pressure, heart attack, and even death because your body cannot respond to any stress or illness.

Your doctor may do special blood and urine tests to check your adrenal gland function while you are using CLOBEX® Lotion.

Other possible side effects with CLOBEX® Lotion include mild burning, stinging, itching, redness, irritation, and dry skin. Also, thinning of the skin, widening of small blood vessels in the skin, and skin discomfort at the site of application may happen. Sometimes your condition will get worse with use of CLOBEX® Lotion.

If you are ill or injured, or going to have surgery, tell your doctor that you are using CLOBEX® Lotion.

Tell your doctor if you:

- are going to have surgery
- get sick or don’t feel right. Call your doctor right away.
- have irritation of the treated skin area that does not go away.
- have any unusual effects that you do not understand.
- have affected areas that do not seem to be getting better after 2 weeks of using CLOBEX® Lotion.

These are not all the possible side effects of CLOBEX® Lotion. For more information, ask your doctor or pharmacist.

General information about the safe and effective use of CLOBEX® Lotion.

Medicines are sometimes prescribed for conditions that are not mentioned in patient information leaflets. Do not use CLOBEX® Lotion for a condition for which it was not prescribed. Do not give CLOBEX® Lotion to other people, even if they have the same symptoms you have. It may harm them. Keep CLOBEX® Lotion and all medicines out of reach of children.

This leaflet summarizes the most important information about CLOBEX® Lotion. If you would like more information, talk with your doctor. You can ask your pharmacist or doctor for information about CLOBEX® Lotion that is written for health professionals.

What are the ingredients of CLOBEX® Lotion?

Active Ingredient: clobetasol propionate

Inactive Ingredients: hypromellose, propylene glycol, mineral oil, polyoxyethylene glycol 300 isostearate, carbomer 1342, sodium hydroxide and purified water.

Rx Only

US Patent No. 6,106,848

Marketed by:
GALDERMA LABORATORIES, L.P.
Fort Worth, Texas 76177 USA

Manufactured by:
DPT Laboratories, Ltd.
San Antonio, Texas 78215 USA

GALDERMA is a registered trademark.

www.clobex.com

325070-1005

Revised: October 2005

PRINCIPAL DISPLAY PANEL

Rx Only

Clobex®
(clobetasol propionate)

LOTION

0.05%

4 FL OZ (118 mL)

For external use only. Not for eye use.

Usual dosage: Apply twice daily, once in the morning and once at night. Use only enough to cover the affected areas. Do not apply Clobex® Lotion, 0.05% to the face, underarms, or groin and avoid contact with eyes and lips. See package insert for complete prescribing information.

Each gram contains: Active: clobetasol propionate 0.5 mg. Inactive: hypromellose, polyoxyethylene glycol 300 isostearate, carbomer 1342, mineral oil, propylene glycol, sodium hydroxide, and purified water.

Store at controlled room temperature 68° to 77°F (20° - 25°C). Protect from freezing. See lot no. and expiration date on bottom of bottle.